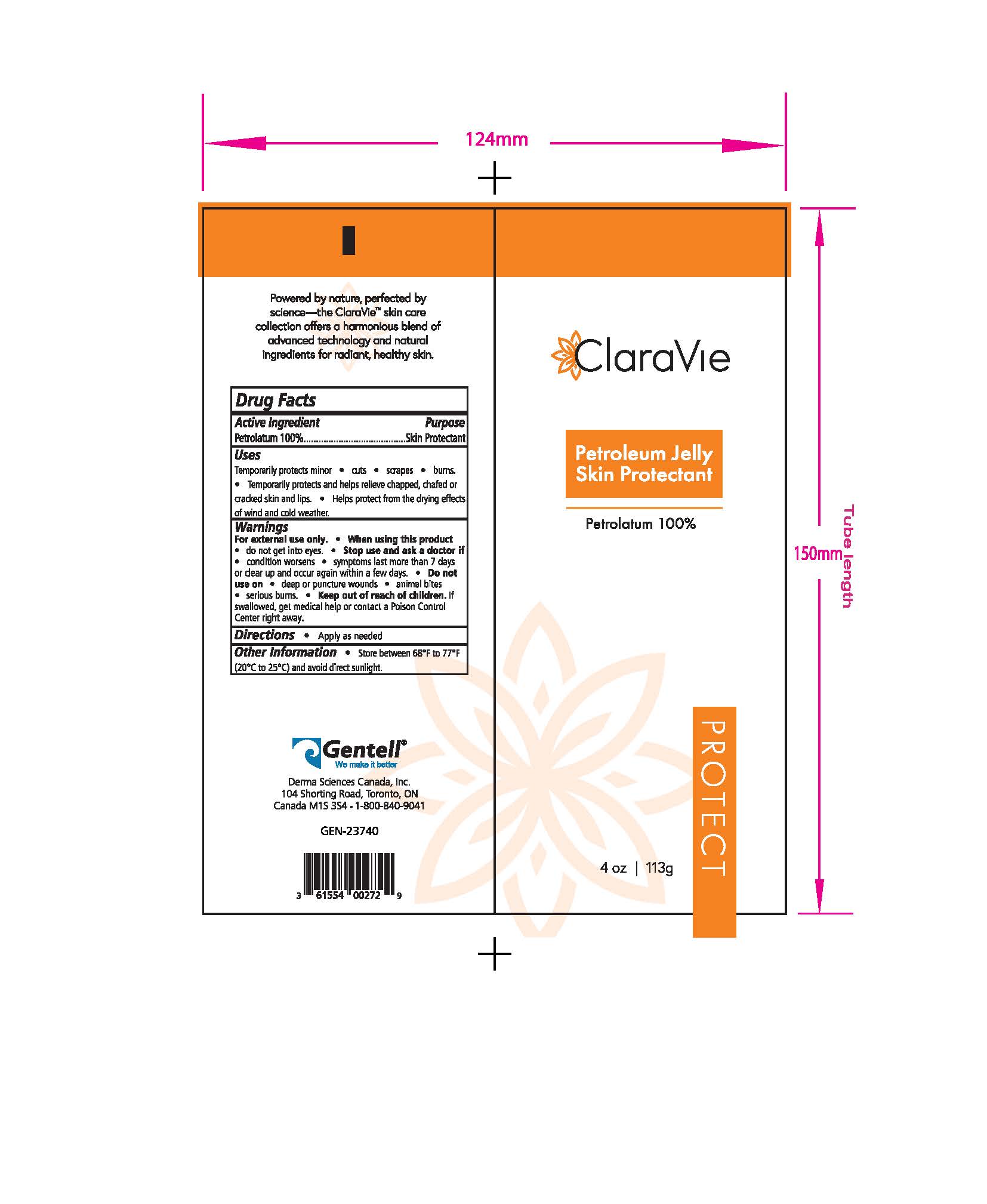 DRUG LABEL: Petroleum Jelly
NDC: 64772-202 | Form: JELLY
Manufacturer: Derma Sciences Canada Inc.
Category: otc | Type: HUMAN OTC DRUG LABEL
Date: 20250722

ACTIVE INGREDIENTS: PETROLATUM 1 g/1 g

Petroleum Jelly

Active Ingredient

Petrolatum 100% ......................................... Skin Protectant

PURPOSE

Skin Protectant

Warnings

For external use only •When using this product• do not get into eyes • Stop use and ask a doctor if

• condition worsens • symptoms last more than 7 days or clear up and occur again within a few days. • Do not
use on • deep or puncture wounds • animal bites • serious burns. . Keep out of reach of children. If
swallowed, get medical help or contact a Poison Control Center right away.

Stop use and ask a doctor if • condition worsens • symptoms last more than 7 days or clear up and occur again within a few days.

Other Information .

Store between 68° F to 77° F (20° to 25°() and avoid direct sunlight.

Directions

Apply as needed

DOSAGE AND ADMINISTRATION

apply as needed

No inactive ingredients. Not applicable

Uses
Temporarily protects minor . cuts . scrapes . burns. Temporarily protects and helps relieve chapped, chafed or cracked skin and lips. Helps protect from the frying effect of wind and cold weather.

KEEP OUT OF REACH OF CHILDREN

If swallowed, get medical help or contact a Poison Control Center right away.